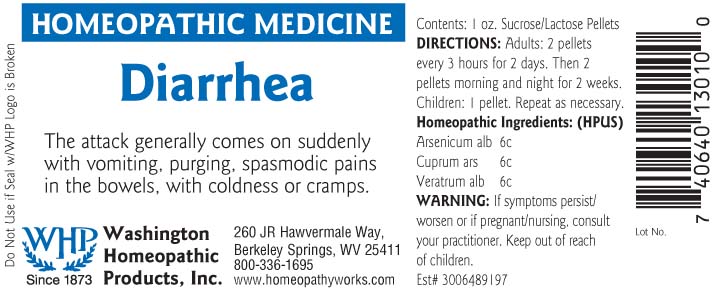 DRUG LABEL: Diarrhea
NDC: 68428-002 | Form: PELLET
Manufacturer: Washington Homeopathic Products
Category: homeopathic | Type: HUMAN OTC DRUG LABEL
Date: 20191223

ACTIVE INGREDIENTS: ARSENIC TRIOXIDE 6 [hp_C]/28 g; CUPRIC ARSENITE 6 [hp_C]/28 g; VERATRUM ALBUM ROOT 6 [hp_C]/28 g
INACTIVE INGREDIENTS: SUCROSE; LACTOSE

DRUG FACTS

ACTIVE INGREDIENTS

ARSENICUM ALBUM 6C

CUPRUM ARSENICUM 6C

VERATRUM ALBUM 6C

USES

For the temporary relief of symptoms related to diarrhea such us: watery stool, abdominal pain, nausea.

KEEP OUT OF REACH OF CHILDREN

Keep this and all medicines out of reach of children.

INDICATIONS

Indications: Arsenicum Album, Food poisoning;

Cuprum Arsenicosum, Leg cramps;

Veratrum Album, Collapse.

STOP USE AND ASK DOCTOR

If symptoms persist/worsen or if pregnant/nursing, stop use and consult your practitioner.

DIRECTIONS

Adults 2 pellets every 3 hours for 2 days. Then 2 pellets morning and night for 2 weeks.

Children: 1 pellet. Repeat as necessary.

INACTIVE INGREDIENTS

Sucrose/Lactose

PRINCIPAL DISPLAY PANEL

Enter section text here